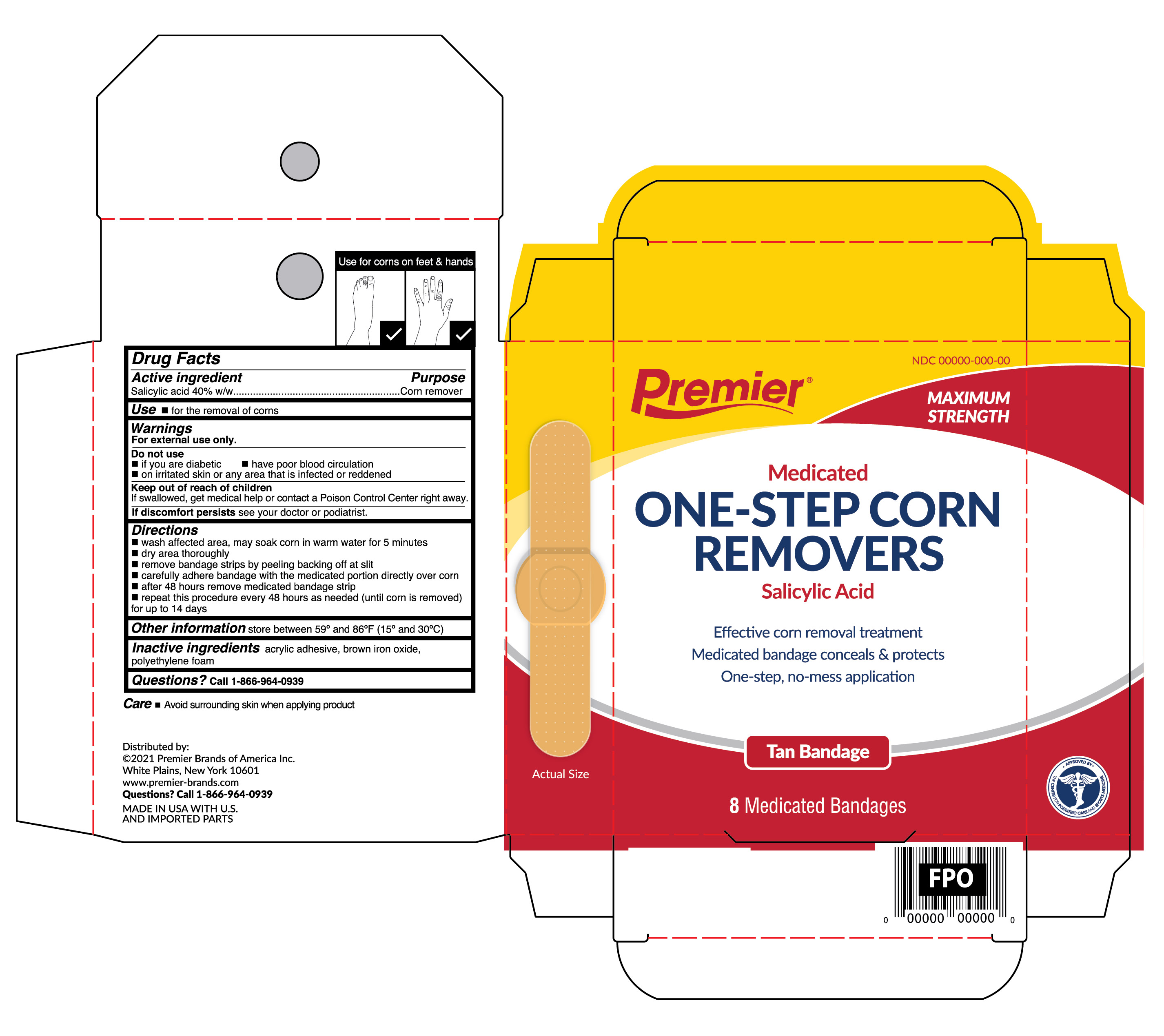 DRUG LABEL: Salicylic Acid
NDC: 56104-047 | Form: PATCH
Manufacturer: Premier Brands of America Inc.
Category: otc | Type: HUMAN OTC DRUG LABEL
Date: 20210201

ACTIVE INGREDIENTS: SALICYLIC ACID 40 mg/6 1
INACTIVE INGREDIENTS: HIGH DENSITY POLYETHYLENE; BROWN IRON OXIDE

Premier Brands One-Step Corn Removers Tan

Active ingredient

Salicylic acid 40%w/w

Purpose

Corn remover

Use

- for the removal of corns

Warnings

For external use only.

Do not use

- if you are a diabetic
- have poor blood circulation
- on irritated skin or any area that is infected or reddened

Keep out of reach of children

If swallowed, get medical help or contact a Poison Control Center right away.

STOP USE

If discomfort persists see your doctor or podiatrist.

Directions

- wash affected area: may soak corn in warm water for 5 minutes
- dry area thoroughly
- remove bandage strips by peeling backing off at slit
- carefully adhere bandage with the medicated portion directly over corn
- after 48 hours remove medicated bandage strip
- repeat this procedure every 48 hours as needed (until corn is removed) for up to 14 days

Other information

store between 59° to 86°F (15° to 30°C)

Inactive ingredients

acrylic adhesive, brown iron oxide, polyethylene foam

Questions?

call 1-866-964-0939

Principal Display Panel

Premier

Medicated

ONE-STEP CORN

REMOVERS

Salicylic Acid

Effective corn removal treatment

Medicated bandage conceals & protects

One-step, no mess application

Tan Bandage

8 Medicated Bandages